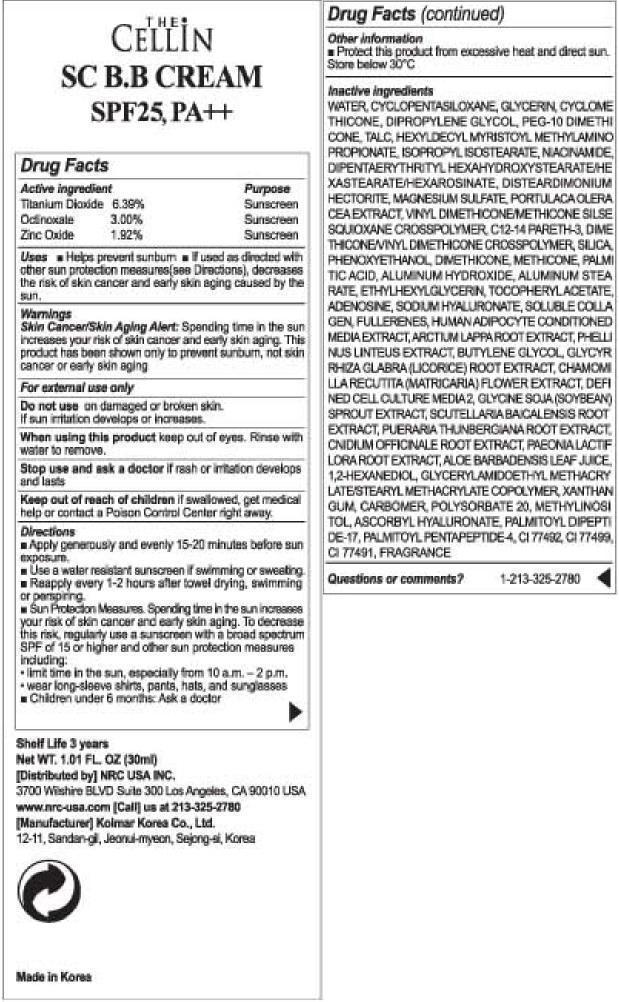 DRUG LABEL: The Cellin SC BB Cream SPF 25 PA
                
                
NDC: 76173-1100 | Form: CREAM
Manufacturer: Cellinbio Co Ltd
Category: otc | Type: HUMAN OTC DRUG LABEL
Date: 20130828

ACTIVE INGREDIENTS: TITANIUM DIOXIDE 6.39 g/30 g; OCTINOXATE 3.00 g/30 g; ZINC OXIDE 1.92 g/30 g
INACTIVE INGREDIENTS: WATER; CYCLOMETHICONE 5; GLYCERIN; CYCLOMETHICONE; DIPROPYLENE GLYCOL; PEG-10 DIMETHICONE (600 CST); TALC; HEXYLDECYL MYRISTOYL METHYLAMINOPROPIONATE; ISOPROPYL ISOSTEARATE; NIACINAMIDE; DISTEARDIMONIUM HECTORITE; MAGNESIUM SULFATE; FERRIC OXIDE YELLOW; PURSLANE; C12-14 PARETH-3; DIMETHICONE/VINYL DIMETHICONE CROSSPOLYMER (HARD PARTICLE); SILICON DIOXIDE; PHENOXYETHANOL; DIMETHICONE; METHICONE (20 CST); FERROSOFERRIC OXIDE; PALMITIC ACID; FERRIC OXIDE RED; ALUMINUM HYDROXIDE; ALUMINUM STEARATE; ETHYLHEXYLGLYCERIN; .ALPHA.-TOCOPHEROL ACETATE; ADENOSINE; HYALURONATE SODIUM; BUCKMINSTERFULLERENE; ARCTIUM LAPPA ROOT; BUTYLENE GLYCOL; GLYCYRRHIZA GLABRA; CHAMOMILE; SOYBEAN; SCUTELLARIA BAICALENSIS ROOT; PUERARIA MONTANA VAR. LOBATA ROOT; CNIDIUM OFFICINALE ROOT; PAEONIA LACTIFLORA ROOT; ALOE VERA LEAF; 1,2-HEXANEDIOL; XANTHAN GUM; POLYSORBATE 20; METHYLINOSITOL; PALMITOYL PENTAPEPTIDE-4

The Cellin SC BB Cream SPF25 PA

Drug Facts

Titanium Dioxide 6.39%
Octinoxate 3.00%
Zinc Oxide 1.92%

Purpose

Sunscreen

Keep out of reach of children if swallowed, get medical help or contact a Poison Control Center right away.

Indication & Usage

Directions
■ Apply generously and evenly 15-20 minutes before sun exposure.
■ Use a water resistant sunscreen if swimming or sweating.
■ Reapply every 1-2 hours after towel drying, swimming or perspiring.
■ Sun Protection Measures. Spending time in the sun increases your risk of skin cancer and early skin aging. To decrease this risk, regularly use a sunscreen with a broad spectrum SPF of 15 or higher and other sun protection measures including:
• limit time in the sun, especially from 10 a.m. – 2 p.m.
• wear long-sleeve shirts, pants, hats, and sunglasses
■ Children under 6 months: Ask a doctor

Warnings

Skin Cancer/Skin Aging Alert: Spending time in the sun increases your risk of skin cancer and early skin aging. This product has been shown only to prevent sunburn, not skin cancer or early skin aging
For external use only
Do not use on damaged or broken skin. If sun irritation develops or increases.
When using this product keep out of eyes. Rinse with water to remove.
Stop use and ask a doctor if rash or irritation develops and lasts

Dosage & Administration

Uses
■ Helps prevent sunburn
■ If used as directed with other sun protection measures(see Directions), decreases the risk of skin cancer and early skin aging caused by the sun.

Inactive Ingredient

WATER, CYCLOPENTASILOXANE, GLYCERIN, CYCLOMETHICONE, DIPROPYLENE GLYCOL, PEG-10 DIMETHICONE, TALC, HEXYLDECYL MYRISTOYL METHYLAMINOPROPIONATE, ISOPROPYL ISOSTEARATE, NIACINAMIDE, DIPENTAERYTHRITYL HEXAHYDROXYSTEARATE/HEXASTEARATE/HEXAROSINATE, DISTEARDIMONIUM HECTORITE, MAGNESIUM SULFATE, PORTULACA OLERACEA EXTRACT, VINYL DIMETHICONE/METHICONE SILSESQUIOXANE CROSSPOLYMER, C12-14 PARETH-3, DIMETHICONE/VINYL DIMETHICONE CROSSPOLYMER, SILICA, PHENOXYETHANOL, DIMETHICONE, METHICONE, PALMITIC ACID, ALUMINUM HYDROXIDE, ALUMINUM STEARATE, ETHYLHEXYLGLYCERIN, TOCOPHERYL ACETATE, ADENOSINE, SODIUM HYALURONATE, SOLUBLE COLLAGEN, FULLERENES, HUMAN ADIPOCYTE CONDITIONED MEDIA EXTRACT, ARCTIUM LAPPA ROOT EXTRACT, PHELLINUS LINTEUS EXTRACT, BUTYLENE GLYCOL, GLYCYRRHIZA GLABRA (LICORICE) ROOT EXTRACT, CHAMOMILLA RECUTITA (MATRICARIA) FLOWER EXTRACT, DEFINED CELL CULTURE MEDIA 2, GLYCINE SOJA (SOYBEAN) SPROUT EXTRACT, SCUTELLARIA BAICALENSIS ROOT EXTRACT, PUERARIA THUNBERGIANA ROOT EXTRACT, CNIDIUM OFFICINALE ROOT EXTRACT, PAEONIA LACTIFLORA ROOT EXTRACT, ALOE BARBADENSIS LEAF JUICE, 1,2-HEXANEDIOL, GLYCERYLAMIDOETHYL METHACRYLATE/STEARYL METHACRYLATE COPOLYMER, XANTHAN GUM, CARBOMER, POLYSORBATE 20, METHYLINOSITOL, ASCORBYL HYALURONATE, PALMITOYL DIPEPTIDE-17, PALMITOYL PENTAPEPTIDE-4, CI 77492, CI 77499, CI 77491, FRAGRANCE

The Cellin SC BB Cream SPF25 PA

Net WT. 1.01 FL OZ (30ml)